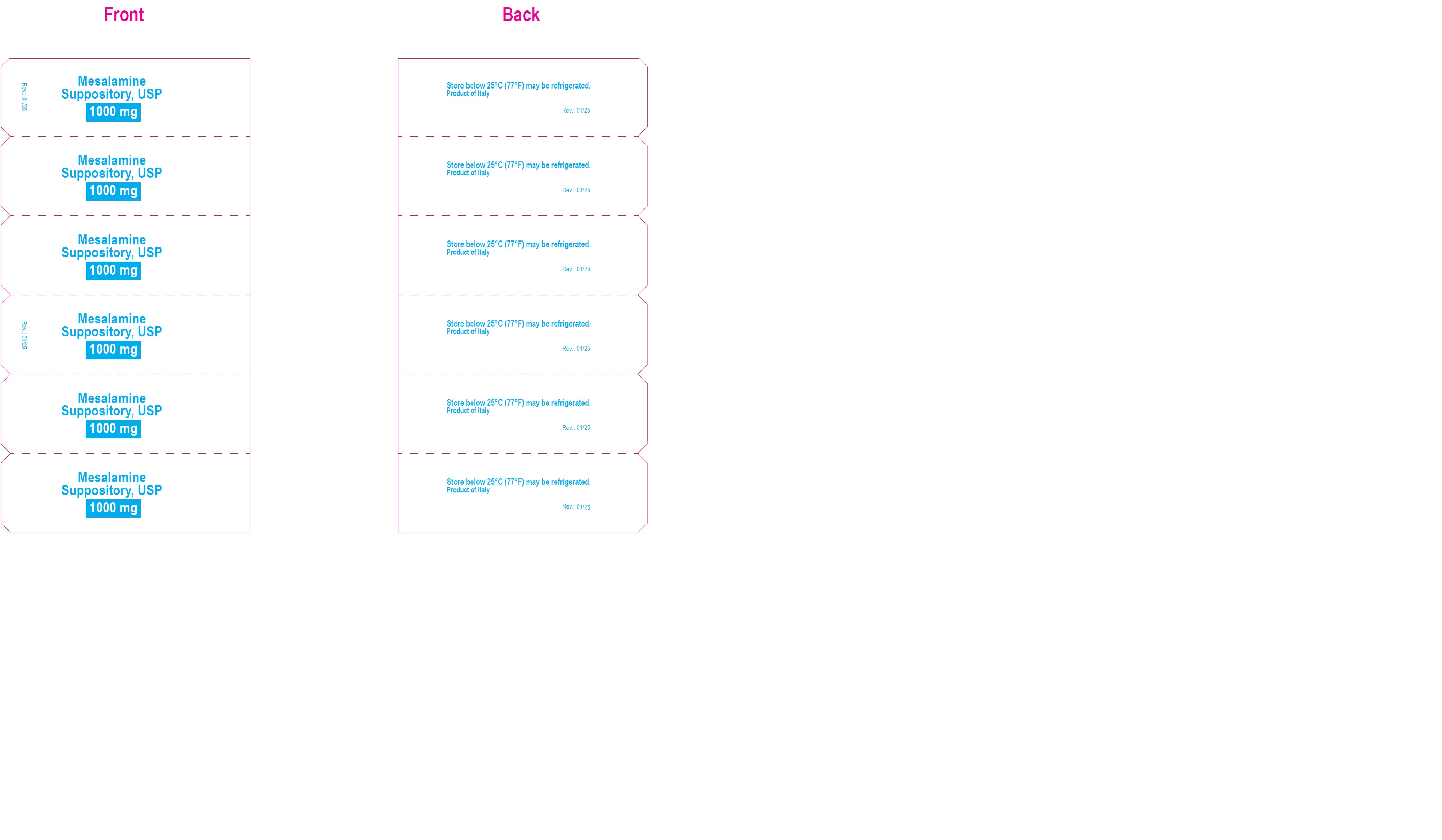 DRUG LABEL: Mesalamine
NDC: 70771-1513 | Form: SUPPOSITORY
Manufacturer: Zydus Lifesciences Limited
Category: prescription | Type: HUMAN PRESCRIPTION DRUG LABEL
Date: 20250109

ACTIVE INGREDIENTS: MESALAMINE 1000 mg/1 1
INACTIVE INGREDIENTS: FAT, HARD

MESALAMINE SUPPOSITORIES

PACKAGE LABEL.PRINCIPAL DISPLAY PANEL

NDC 70771-1513-6

Mesalamine suppositories, 1000 mg

30 rectal suppositories

Rx only

Image